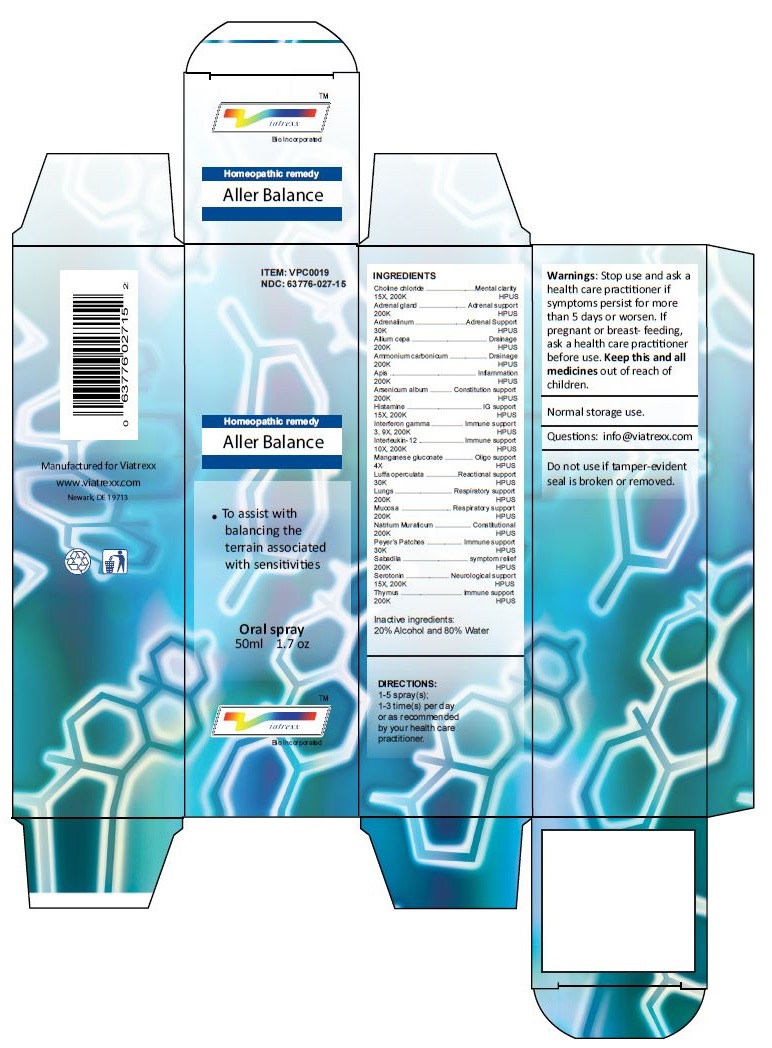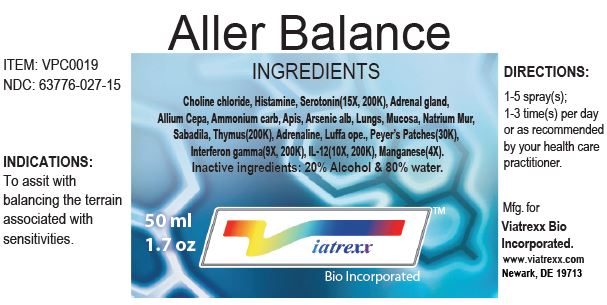 DRUG LABEL: Aller Balance
NDC: 63776-027 | Form: SPRAY
Manufacturer: VIATREXX BIO INCORPORATED
Category: homeopathic | Type: HUMAN OTC DRUG LABEL
Date: 20221130

ACTIVE INGREDIENTS: CHOLINE CHLORIDE 200 [kp_C]/1 mL; BOS TAURUS ADRENAL GLAND 200 [kp_C]/1 mL; SUS SCROFA ADRENAL GLAND 200 [kp_C]/1 mL; EPINEPHRINE 30 [kp_C]/1 mL; ONION 200 [kp_C]/1 mL; AMMONIUM CARBONATE 200 [kp_C]/1 mL; APIS MELLIFERA 200 [kp_C]/1 mL; ARSENIC TRIOXIDE 200 [kp_C]/1 mL; HISTAMINE 200 [kp_C]/1 mL; INTERFERON GAMMA-1A 200 [kp_C]/1 mL; INTERLEUKIN-12 HUMAN 200 [kp_C]/1 mL; MANGANESE GLUCONATE 4 [hp_X]/1 mL; LUFFA OPERCULATA FRUIT 30 [kp_C]/1 mL; SUS SCROFA LUNG 200 [kp_C]/1 mL; BEEF LUNG 200 [kp_C]/1 mL; SUS SCROFA NASAL MUCOSA 200 [kp_C]/1 mL; BOS TAURUS NASAL MUCOSA 200 [kp_C]/1 mL; SODIUM CHLORIDE 200 [kp_C]/1 mL; BOS TAURUS PEYER'S PATCH 30 [kp_C]/1 mL; SUS SCROFA PEYER'S PATCH 30 [kp_C]/1 mL; SCHOENOCAULON OFFICINALE SEED 200 [kp_C]/1 mL; SEROTONIN 200 [kp_C]/1 mL; BOS TAURUS THYMUS 200 [kp_C]/1 mL; SUS SCROFA THYMUS 200 [kp_C]/1 mL
INACTIVE INGREDIENTS: ALCOHOL; WATER

Aller Balance

Active Ingredients

Choline chloride (15X, 200K), Histamine (15X, 200K), Serotonin (15X, 200K), Adrenal gland (200K), Allium Cepa (200K), Ammonium carbonicum (200K), Apis (200K), Arsenicum album (200K), Lungs (200K), Mucosa (200K), Natrium Mur (200K), Sabadila (200K), Thymus (200K), Adrenalinum (30K), Luffa operculata (30K), Peyer's Patches (30K), Interferon gamma (9X, 200K), Interleukin-12 (10X, 200K), Manganese gluconate (4X)

Purpose:

Choline chloride | Mental clarity
Adrenal gland | Adrenal support
Adrenalinum | Adrenal support
Allium cepa | Drainage
Ammonium carbonicum | Drainage
Apis | Inflammation
Arsenicum album | Constitution support
Histamine | IG support
Interferon gamma | Immune support
Interleukin-12 | Immune support
Manganese gluconate | Oligo support
Luffa operculata | Reactional support
Lungs | Respiratory support
Mucosa | Respiratory support
Natrium Muraticum | Constitutional
Peyer's Patch | Immune support
Sabadila | symptom relief
Serotonin | Neurological support
Thymus | Immune support

Uses

To assist with balancing the terrain associated with sensitivities

Warnings

Stop use and ask a health care practitioner if symptoms persist for more than five days or worsen. If pregnant or breastfeeding, ask a health care practitioner before use.

Dosage

1-5 spray(s); 1-3 time(s) per day or as recommended by your health care practitioner.

KEEP OUT OF REACH OF CHILDREN

Keep this and all medicines out of reach of children.

Other Ingredients

20% Alcohol and 80% Water.

Other Information

Normal storage use.
Do not use if tamper-evident seal is broken or removed.

Questions

info@viatrexx.com

Principal Display Panel

ITEM: VPC0019
NDC 63776-027-15
Homeopathic remedy
Aller Balance
• To assist with balancing the terrain associated with sensitivities
Oral spray
50ml 1.7 oz
Viatrexx™ Bio Incorporated
Manufactured by Viatrexx
www.viatrexx.com
Newark, DE 19713

Aller Balance
50 ml
1.7 oz
Viatrexx™ Bio Incorporated
ITEM: VPC0019
NDC: 63776-027-15
INDICATIONS:
To assit with balancing the terrain associated with sensitivities.
DIRECTIONS:
1-5 spray(s); 1-3 time(s) per day or as recommended by your health care practitioner.
Mfg. for
Viatrexx Bio Incorporated.
www.viatrexx.com
Newark, DE 19713